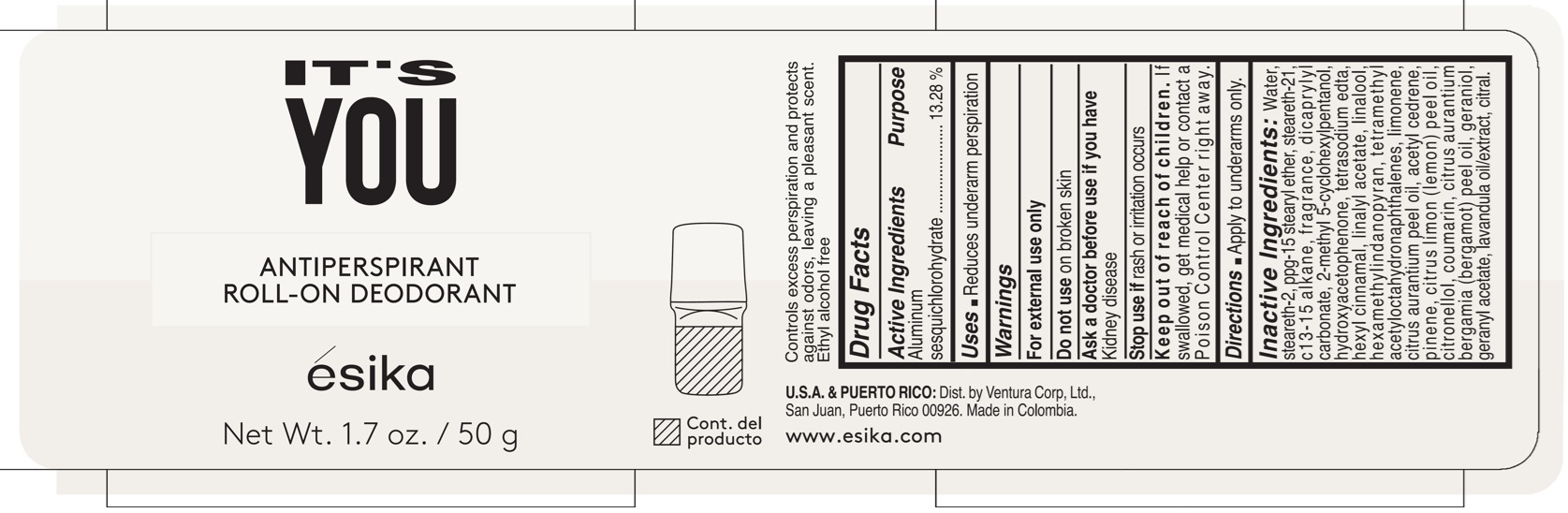 DRUG LABEL: ESIKA ITS YOU ANTIPERSPIRANT ROLL-ON DEODORANT
NDC: 14141-363 | Form: EMULSION
Manufacturer: BEL STAR S.A.
Category: otc | Type: HUMAN OTC DRUG LABEL
Date: 20241203

ACTIVE INGREDIENTS: ALUMINUM SESQUICHLOROHYDRATE 132.8 mg/1 g
INACTIVE INGREDIENTS: CITRONELLOL; CITRUS AURANTIUM BERGAMIA (BERGAMOT) PEEL OIL; LINALYL ACETATE; COUMARIN; GERANIOL; CITRAL; C13-15 ALKANE; GERANYL ACETATE; WATER; PPG-15 STEARYL ETHER; STEARETH-2; STEARETH-21; HEXYL CINNAMAL; DICAPRYLYL CARBONATE; HYDROXYACETOPHENONE; HEXAMETHYLINDANOPYRAN; CITRUS AURANTIUM PEEL OIL; EDETATE SODIUM; ACETYL CEDRENE; PINENE; LEMON OIL; LINALOOL, (+/-)-; LIMONENE, (+)-; TETRAMETHYL ACETYLOCTAHYDRONAPHTHALENES; 2-METHYL 5-CYCLOHEXYLPENTANOL; LAVENDER OIL

ÉSIKA IT'S YOU ANTIPERSPIRANT ROLL-ON DEODORANT

Active Ingredients

Aluminum sesquichlorohydrate 13.28%

Purpose

Antiperspirant

Uses

- Reduces underarm perspiration

Warnings

For external use only

Do not use

on broken skin

Ask a doctor before use if you have

kidney desease

Stop use if

rash or irritation occurs

Keep out of reach of children.

If swallowed, get medical help or contact a Poison Control Center right away.

Directions

- Apply to underarms only.

Inactive Ingredients

Water, steareth-2, ppg-15 stearyl ether, steareth-21, c13-15 alkane, fragrance, dicaprylyl carbonate, 2-methyl 5-cyclohexylpentanol, hydroxyacetophenone, tetrasodium edta, hexyl cinnamal, linalyl acetate, linalool, hexamethylindanopyran, tetramethyl acetyloctahydronaphthalenes, limonene, citrus aurantium peel oil, acetyl cedrene, pinene, citrus limon (lemon) peel oil, citronellol, coumarin, citrus aurantium bergamia (bergamot) peel oil, geraniol, geranyl acetate, lavandula oil/extract, citral.

Company Information

Dist. by Ventura Corp, Ltd., San Juan, Puerto Rico 00926.